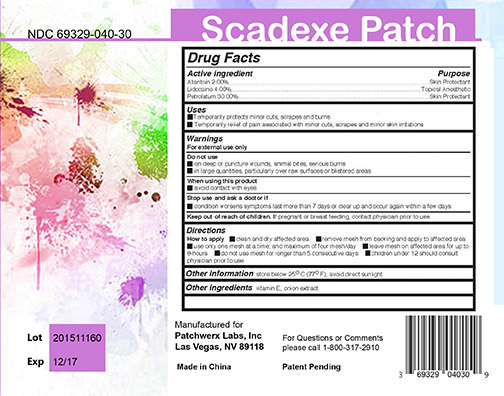 DRUG LABEL: SCADEXE
NDC: 69329-040 | Form: PATCH
Manufacturer: Patchwerx Labs, Inc.
Category: otc | Type: HUMAN OTC DRUG LABEL
Date: 20150415

ACTIVE INGREDIENTS: LIDOCAINE HYDROCHLORIDE 4 g/100 g; PETROLATUM 30 g/100 g; ALLANTOIN 2 g/100 g
INACTIVE INGREDIENTS: ONION; ALPHA-TOCOPHEROL

SCADEXE PATCH

Active Ingredient Section

Active Ingredient

Allantoin 2.00 %

Lidocaine 4.00 %

Petrolatum 30.00 %

ASK DOCTOR SECTION

Stop use and ask a doctor if condition worsens, symptoms persist for more than 7 days or clear up and occur again within a few days

DO NOT USE SECTION

- on deep or puncture wounds, animal bites, serious burns

- in large quantities, particularly over raw surfaces or blistered areas

Keep out of reach of children. If pregnant or breastfeeding, contact physician prior to use

PREGNANCY OR BREAST FEEDING

If pregnant or breastfeeding, contact physician prior to use

PURPOSE

- Temporarily protects minor cuts , scrapes and burns

- Temporary relief of pain associated with minor cuts, scrapes and minor skin irritations

QUESTIONS

For questions or comments please call 800-317-2910

STOP USE SECTION

Stop use if condition worsens, symptoms persist for more than 7 days or clear up and occur again within a few days.

WHEN USING SECTION

How to apply

- clean and dry affected area

- remove mesh from backing and apply to affected area

- use only one mesh at a time, and maximum of four mesh / day

- leave mesh on affected area for up to 8 hours

- children under 12 should consult

Warnings

Stop use if condition worsens, symptoms persist for more than 7 days or clear up and occur again within a few days.

Do not use if pregnant.

Keep away from Children

Inactive Ingredients These highlights do not include all the information needed to use

ONION

ALPHA-TOCOPHEROL